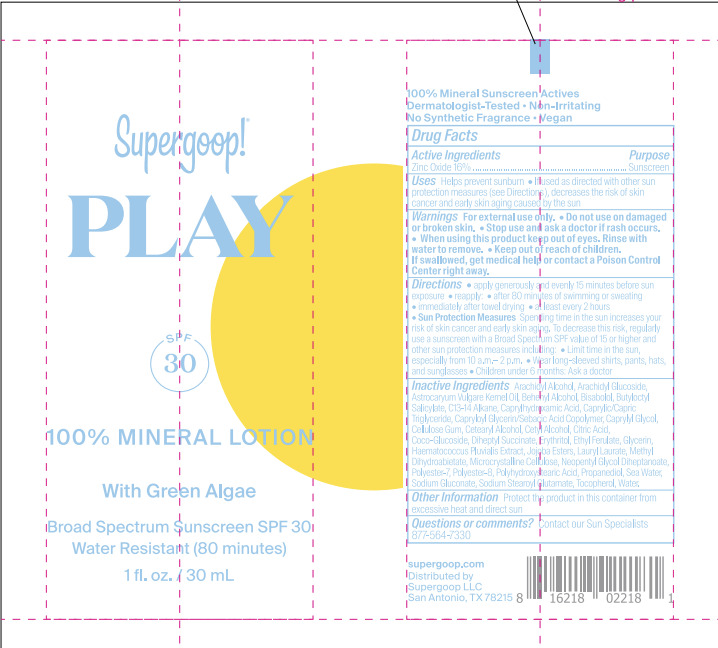 DRUG LABEL: PLAY Mineral SPF 30 with Green Algae
NDC: 75936-651 | Form: LOTION
Manufacturer: Supergoop LLC
Category: otc | Type: HUMAN OTC DRUG LABEL
Date: 20260109

ACTIVE INGREDIENTS: ZINC OXIDE 16 g/100 mL
INACTIVE INGREDIENTS: NEOPENTYL GLYCOL DIHEPTANOATE; DIHEPTYL SUCCINATE; SODIUM GLUCONATE; ANHYDROUS CITRIC ACID; CAPRYLIC/CAPRIC TRIGLYCERIDE; METHYL DIHYDROABIETATE; ASTROCARYUM VULGARE KERNEL OIL; CAPRYLHYDROXAMIC ACID; CAPRYLOYL GLYCERIN/SEBACIC ACID COPOLYMER (2000 MPA.S); SODIUM CHLORIDE; BISABOLOL; WATER; JOJOBA OIL; HAEMATOCOCCUS PLUVIALIS; TETRADECANE; LAURYL LAURATE; POLYHYDROXYSTEARIC ACID (2300 MW); BEHENYL ALCOHOL; TOCOPHEROL; BUTYLOCTYL SALICYLATE; ARACHIDYL ALCOHOL; ARACHIDYL GLUCOSIDE; CAPRYLYL GLYCOL; CELLULOSE, MICROCRYSTALLINE; CELLULOSE GUM; ERYTHRITOL; GLYCERIN; PROPANEDIOL; SODIUM STEAROYL GLUTAMATE; ETHYL FERULATE; POLYESTER-7; CETOSTEARYL ALCOHOL; POLYESTER-8 (1400 MW, CYANODIPHENYLPROPENOYL CAPPED); CETYL ALCOHOL; COCO-GLUCOSIDE

PLAY 100% Mineral Lotion SPF 30 with Green Algae

Active Ingredient: Zinc Oxide 16.0%

PURPOSE

Helps prevent sunburn

If used as directed with other sun protection measures (see Directions), decreases the risk of skin cancer and early skin aging caused by the sun

Keep out of reach of children. If product is swallowed, get medical help, or contact a poison control center right away.

WARNINGS

For External use only

Do not use on damaged or broken skin

When using this product, keep out of eyes. Rinse with water to remove

Stop use and ask a doctor if rash occurs

Directions

Apply generously and evenly 15 minutes before sun exposure

Reapply

- after 80 minutes of swimming or sweating
- Immediately after towel drying
- at least every 2 hours

Sun Protection Measures: Spending time in the sun increases your risk of skin cancer and early skin aging. To decrease this risk, regularly use a sunscreen with a Broad Spectrum SPF value of 15 or higher and other sun protection measures including:

- Limit time in the sun, especially from 10 a.m.- 2 p.m.
- Wear long-sleeved shirts, pants, hats, and sunglasses
- Children under 6 months: Ask a doctor

INACTIVE INGREDIENT

Water, Caprylic/Capric Triglyceride, Butyloctyl Salicylate, Erythritol,Lauryl Laurate, Methyl Dihydroabietate, Jojoba Esters, Diheptyl Succinate, Propanediol, Sodium Stearoyl Glutamate, Cetearyl Alcohol, Polyester-7, Capryloyl Glycerin/Sebacic Acid Copolymer, Microcrystalline Cellulose, C13-14 Alkane, Arachidyl Alcohol, Neopentyl Glycol Diheptanoate, Water, Tocopherol, Cetyl Alcohol, Caprylyl Glycol, Coco-Glucoside, Behenyl Alcohol, Ethyl Ferulate, Polyester-8, Bisabolol, Polyhydroxystearic Acid, Arachidyl Glucoside, Astrocaryum Vulgare Kernel Oil, Haematococcus Pluvialis Extract, Sodium Gluconate, Citric Acid, Caprylhydroxamic Acid, Glycerin, Cellulose Gum, Sea Water, Tocopherol,

PACKAGE LABEL

Supergoop!

PLAY

100% Mineral Lotion

SPF 30

With Green Algae

Broad Spectrum Sunscreen SPF 30

Water Resistant (80 minutes)

1 fl. oz./30 mL